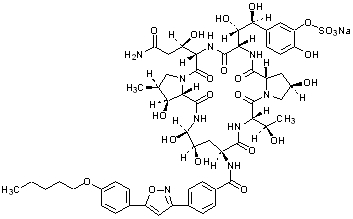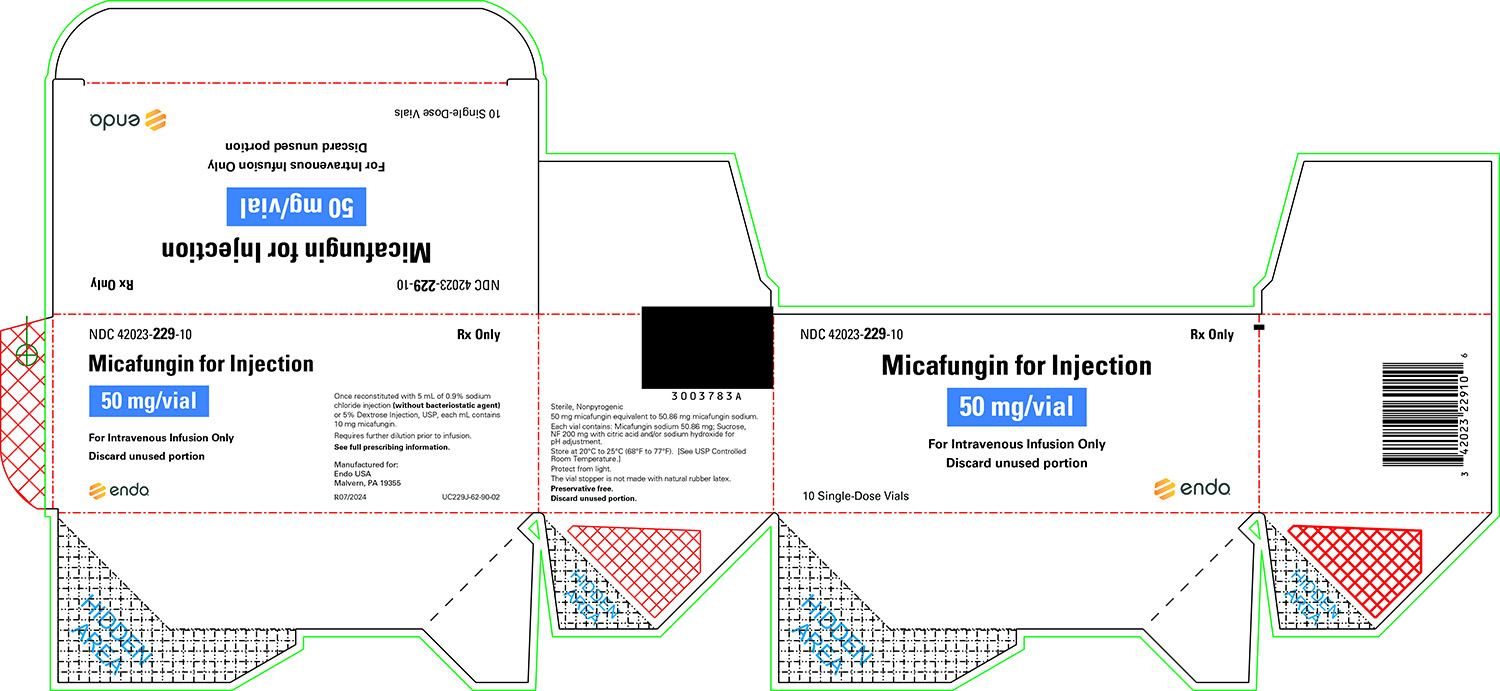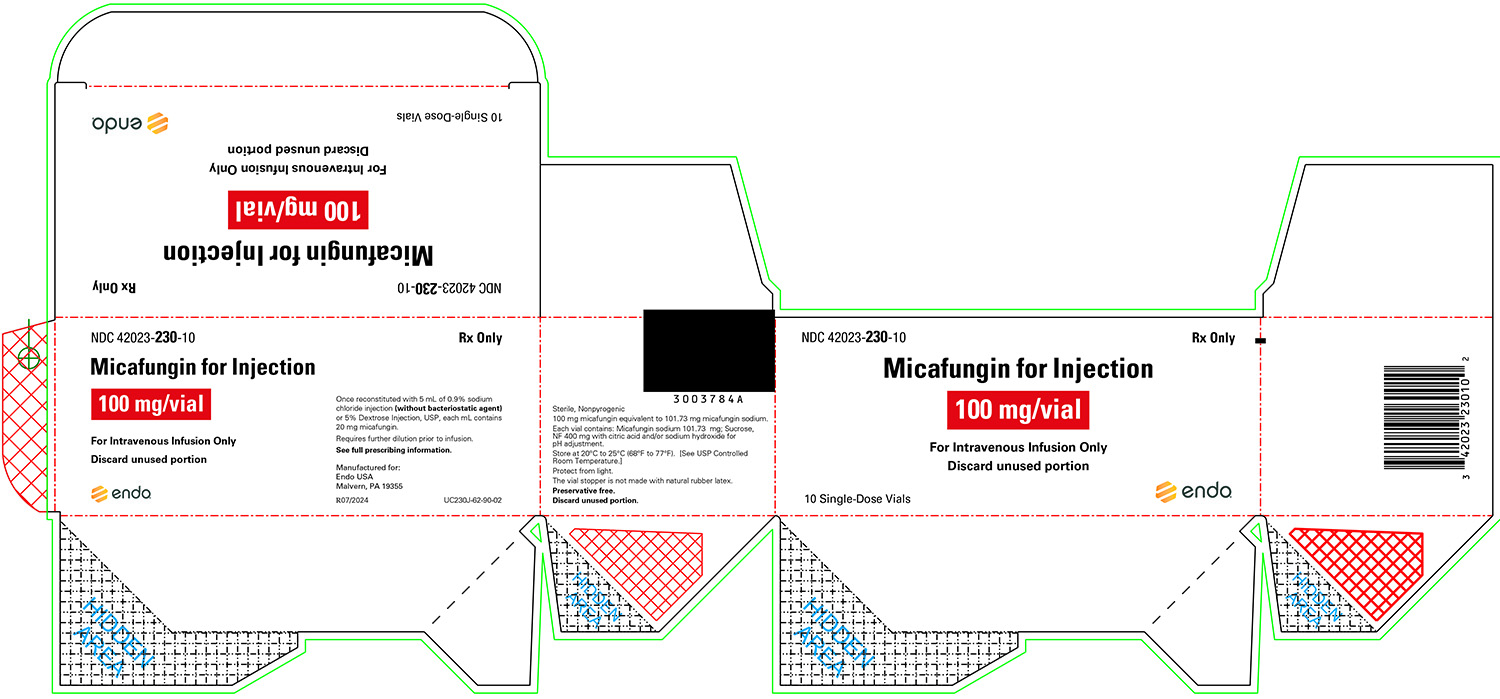 DRUG LABEL: Micafungin
NDC: 42023-229 | Form: INJECTION, POWDER, LYOPHILIZED, FOR SOLUTION
Manufacturer: Par Health USA, LLC
Category: prescription | Type: HUMAN PRESCRIPTION DRUG LABEL
Date: 20210605

ACTIVE INGREDIENTS: MICAFUNGIN SODIUM 10 mg/1 mL
INACTIVE INGREDIENTS: CITRIC ACID MONOHYDRATE; SODIUM HYDROXIDE

HIGHLIGHTS OF PRESCRIBING INFORMATION

These highlights do not include all the information needed to use MICAFUNGIN FOR INJECTION safely and effectively. See full prescribing information for MICAFUNGIN FOR INJECTION.
MICAFUNGIN for injection, for intravenous use
Initial U.S. Approval: 2005 [Additional pediatric use information is approved for Astellas Pharma US, Inc.’s Mycamine® (micafungin for injection). However, due to Astellas Pharma US, Inc.’s marketing exclusivity rights, this drug product is not labeled with that information.]

1 INDICATIONS AND USAGE

Micafungin for Injection is an echinocandin indicated in adult and pediatric patients for:

- Treatment of Candidemia, Acute Disseminated Candidiasis, Candida Peritonitis and Abscesses in adult and pediatric patients 4 months of age and older. (1)
- Treatment of Esophageal Candidiasis in adult and pediatric patients 4 months of age and older. (1)
- Prophylaxis of Candida Infections in adult and pediatric patients 4 months of age and older undergoing Hematopoietic Stem Cell Transplantation (HSCT). (1)

Limitations of Use

- Micafungin for injection has not been adequately studied in patients with endocarditis, osteomyelitis or meningoencephalitis due to Candida. (1)
- The efficacy of Micafungin for Injection against infections caused by fungi other than Candida has not been established. (1)

2 DOSAGE AND ADMINISTRATION

Recommended Dosage Administered by Indication, Weight and Age (2.1, 2.2, 8.4)

Adult | Pediatric Patients 4 Months and Older; 30 kg or less | Pediatric Patients; 4 Months and; Older; greater than; 30 kg
Treatment of Candidemia, Acute Disseminated Candidiasis, Candida Peritonitis and Abscesses
100 mg daily | 2 mg/kg/day; (maximum 100 mg daily)
Treatment of Esophageal Candidiasis
150 mg daily | 3 mg/kg/day | 2.5 mg/kg/day (maximum; 150 mg daily)
Prophylaxis of Candida Infections in HSCT Recipients
50 mg daily | 1 mg/kg/day; (maximum 50 mg daily)

- Infuse over 1 hour. (2.4)
- See full prescribing information for intravenous (IV) preparation and administration instructions. (2)

3 DOSAGE FORMS AND STRENGTHS

- For injection: 50 mg single-dose vial. (3)

- For injection: 100 mg single-dose vial. (3)

4 CONTRAINDICATIONS

Micafungin for Injection is contraindicated in persons with known hypersensitivity to micafungin sodium, any component of Micafungin for Injection, or other echinocandins. (4)

5 WARNINGS AND PRECAUTIONS

- Hypersensitivity Reactions: Anaphylaxis and anaphylactoid reactions (including shock) have been observed. Discontinue Micafungin for Injection and administer appropriate treatment. (5.1)

- Hematological Effects: Isolated cases of acute intravascular hemolysis, hemolytic anemia and hemoglobinuria have been reported. Monitor rate of hemolysis. Discontinue if severe. (5.2)
- Hepatic Effects: Abnormalities in liver tests; isolated cases of hepatic impairment, hepatitis, and hepatic failure have been observed. Monitor hepatic function. Discontinue if severe dysfunction occurs. (5.3)
- Renal Effects: Elevations in BUN and creatinine; isolated cases of renal impairment or acute renal failure have been reported. Monitor renal function. (5.4)
- Infusion and Injection Site Reactions can occur including rash, pruritus, facial swelling, and vasodilatation. Monitor infusion closely, slow infusion rate if necessary. (2.4, 5.5)

6 ADVERSE REACTIONS

- Most common adverse reactions across adult and pediatric clinical trials for all indications include diarrhea, nausea, vomiting, abdominal pain, pyrexia, thrombocytopenia, neutropenia, and headache. (6.1)

To report SUSPECTED ADVERSE REACTIONS, contact Endo at 1-800-828-9393 or FDA at 1-800-FDA-1088 or www.fda.gov/medwatch.

7 DRUG INTERACTIONS

Monitor for sirolimus, itraconazole or nifedipine toxicity, and dosage of sirolimus, itraconazole or nifedipine should be reduced, if necessary. (7)

8 USE IN SPECIFIC POPULATIONS

Pregnancy: Based on animal data, Micafungin for Injection may cause fetal harm. Advise pregnant women of the risk to the fetus. (8.1)

FULL PRESCRIBING INFORMATION

1 INDICATIONS AND USAGE

Micafungin for Injection is indicated for:

- Treatment of Candidemia, Acute Disseminated Candidiasis, Candida Peritonitis and Abscesses in adult and pediatric patients 4 months of age and older [see Clinical Studies (14.1) and Use in Specific Populations (8.4)].
- Treatment of Esophageal Candidiasis in adult and pediatric patients 4 months of age and older [see Clinical Studies (14.2)].
- Prophylaxis of Candida Infections in adult and pediatric patients 4 months of age and older undergoing hematopoietic stem cell transplantation [see Clinical Studies (14.3)].

Limitations of Use

- Micafungin for Injection has not been adequately studied in patients with endocarditis, osteomyelitis and meningoencephalitis due to Candida.
- The efficacy of Micafungin for Injection against infections caused by fungi other than Candida has not been established.

Additional pediatric use information is approved for Astellas Pharma US, Inc.’s Mycamine® (micafungin for injection). However, due to Astellas Pharma US, Inc.’s marketing exclusivity rights, this drug product is not labeled with that information.

2 DOSAGE AND ADMINISTRATION

2.1 Dosage for Adults

The recommended dosage for adult patients based on indications are shown in Table 1.

Table 1. Micafungin for Injection Dosage in Adult Patients

Indication | Recommended Reconstituted Dose; Once Daily
Treatment of Candidemia, Acute Disseminated Candidiasis, Candida Peritonitis and Abscesses* | 100 mg
Treatment of Esophageal Candidiasis‡ | 150 mg
Prophylaxis of Candida Infections in HSCT Recipients§ | 50 mg

* In patients treated successfully for candidemia and other Candida infections, the mean duration of treatment was 15 days (range 10 to 47 days).

‡ In patients treated successfully for esophageal candidiasis, the mean duration of treatment was 15 days (range 10 to 30 days).

§ In hematopoietic stem cell transplant (HSCT) recipients who experienced success of prophylactic therapy, the mean duration of prophylaxis was 19 days (range 6 to 51 days).

2.2 Dosage for Pediatric Patients 4 Months and Older

The recommended dosage for pediatric patients 4 months of age and older based on indication and weight are shown in Table 2.

Table 2. Micafungin for Injection Dosage in Pediatric Patients (4 Months of Age and Older)

Indication | Dosage for Pediatric Patients 4 Months of Age and Older
Indication | 30 kg or less | Greater than 30 kg
Treatment of Candidemia, Acute Disseminated Candidiasis, Candida Peritonitis and Abscesses | 2 mg/kg once daily; (maximum daily dose 100 mg)
Treatment of Esophageal Candidiasis | 3 mg/kg once daily | 2.5 mg/kg once daily; (maximum daily dose 150 mg)
Prophylaxis of Candida Infections in HSCT Recipients | 1 mg/kg once daily; (maximum daily dose 50 mg)

Additional pediatric use information is approved for Astellas Pharma US, Inc.’s Mycamine® (micafungin for injection). However, due to Astellas Pharma US, Inc.’s marketing exclusivity rights, this drug product is not labeled with that information.

2.3 Directions for Reconstitution, Dilution, Preparation and Storage

Do not mix or co-infuse Micafungin for Injection with other medications. Micafungin for injection has been shown to precipitate when mixed directly with a number of other commonly used medications. Please read this entire section carefully before beginning reconstitution.

Reconstitution

Reconstitute Micafungin for Injection vials by aseptically adding 5 mL of one of the following compatible solutions:

- 0.9% Sodium Chloride Injection, USP (without a bacteriostatic agent)
- 5% Dextrose Injection, USP

To minimize excessive foaming, gently dissolve the micafungin for injection powder by swirling the vial. Do not vigorously shake the vial. Visually inspect the vial for particulate matter.

Micafungin for Injection 50 mg vial: after reconstitution each mL contains 10 mg of micafungin.

Micafungin for Injection 100 mg vial: after reconstitution each mL contains 20 mg of micafungin.

Parenteral drug products should be inspected visually for particulate matter and discoloration prior to administration, whenever solution and container permit. Do not use material if there is any evidence of precipitation or foreign matter. Aseptic technique must be strictly observed in all handling since no preservative or bacteriostatic agent is present in Micafungin for Injection or in the materials specified for reconstitution and dilution.

The reconstituted product should be protected from light and may be stored in the original vial for up to 12 hours at room temperature, 25°C (77°F).

Dilution and Preparation

The diluted solution should be protected from light. It is not necessary to cover the infusion drip chamber or the tubing.

Adult Patients:

1. Add the appropriate volume of reconstituted Micafungin for Injection into 100 mL of 0.9% Sodium Chloride Injection, USP or 100 mL of 5% Dextrose Injection, USP.

2. Appropriately label the bag.

Pediatric Patients:

1. Calculate the total Micafungin for Injection dose in milligrams (mg) by multiplying the recommended pediatric dose (mg/kg) for a given indication [see Table 2] and the weight of the patient in kilograms (kg).

2. To calculate the volume (mL) of drug needed, divide the calculated dose (mg) from step 1 by the final concentration of the selected reconstituted vial(s) (either 10 mg/mL for the 50 mg vial or 20 mg/mL for the 100 mg vial), see example below:

Using 50 mg vials:

Divide the calculated mg dose (from step 1) by 10 mg/mL to determine the volume (mL) needed.

OR

Using 100 mg vials:

Divide the calculated mg dose (from step 1) by 20 mg/mL to determine the volume (mL) needed.

3. Withdraw the calculated volume (mL) of drug needed from the selected concentration and size of reconstituted Micafungin for Injection vial(s) used in Step 2 (ensure the selected concentration and vial size used to calculate the dose is also used to prepare the infusion).

4. Add the withdrawn volume of drug (step 3) to a 0.9% Sodium Chloride Injection, USP or 5% Dextrose Injection, USP intravenous infusion bag or syringe. Ensure that the final concentration of the solution is between 0.5 mg/mL to 4 mg/mL.

To decrease the risk of infusion reactions, concentrations above 1.5 mg/mL should be administered via central catheter [see Warnings and Precautions (5.5)].

5. Appropriately label the infusion bag or syringe. For concentrations above 1.5 mg/mL, if required, label to specifically warn to administer the solution via central catheter.

The diluted infusion bag should be protected from light and may be stored for up to 12 hours at room temperature, 25°C (77°F).

Micafungin for Injection is preservative-free. Discard partially used vials.

Storage of Reconstituted and Diluted Solutions

The combined storage time of the reconstituted solution in the original vial and the diluted solution in the infusion bag should not exceed 12 hours at room temperature, 20°C to 25°C (68°F to 77°F) [see USP Controlled Room Temperature], from the time of reconstitution. This combined storage time, not to exceed 12 hours, includes storage of the reconstituted solution in the original vials, storage of the diluted solution and the duration of the infusion.

Protect the reconstituted solution in the original vials and the diluted solution in the infusion bag from light.

2.4 Infusion Volume and Duration

Administer Micafungin for Injection by intravenous infusion only. Infuse over one hour. More rapid infusions may result in more frequent histamine-mediated reactions [see Warnings and Precautions (5.5)].

Flush an existing intravenous line with 0.9% Sodium Chloride Injection, USP, prior to infusion of Micafungin for Injection.

Pediatric Patients

Micafungin for Injection should be infused over one hour. To decrease the risk of infusion reactions, concentrations above 1.5 mg/mL should be administered via central catheter [see Warnings and Precautions (5.5)].

3 DOSAGE FORMS AND STRENGTHS

Micafungin for Injection is a sterile, white lyophilized powder for reconstitution for intravenous infusion available as:

- 50 mg single-dose vial
- 100 mg single-dose vial

4 CONTRAINDICATIONS

Micafungin for Injection is contraindicated in persons with known hypersensitivity to micafungin, any component of Micafungin for Injection, or other echinocandins.

5 WARNINGS AND PRECAUTIONS

5.1 Hypersensitivity Reactions

Isolated cases of serious hypersensitivity (anaphylaxis and anaphylactoid) reactions (including shock) have been reported in patients receiving micafungin for injection. If these reactions occur, Micafungin for Injection infusion should be discontinued, and appropriate treatment administered.

5.2 Hematological Effects

Acute intravascular hemolysis and hemoglobinuria was seen in a healthy volunteer during infusion of micafungin for injection (200 mg) and oral prednisolone (20 mg). Cases of significant hemolysis and hemolytic anemia have also been reported in patients treated with micafungin for injection. Patients who develop clinical or laboratory evidence of hemolysis or hemolytic anemia during micafungin therapy should be monitored closely for evidence of worsening of these conditions and evaluated for the risk/benefit of continuing Micafungin for Injection therapy.

5.3 Hepatic Effects

Laboratory abnormalities in liver function tests have been seen in healthy volunteers and patients treated with micafungin for injection. In some patients with serious underlying conditions who were receiving micafungin for injection along with multiple concomitant medications, clinical hepatic abnormalities have occurred, and isolated cases of significant hepatic impairment, hepatitis, and hepatic failure have been reported. Patients who develop abnormal liver function tests during micafungin therapy should be monitored for evidence of worsening hepatic function and evaluated for the risk/benefit of continuing Micafungin for Injection therapy.

5.4 Renal Effects

Elevations in BUN and creatinine, and isolated cases of significant renal impairment or acute renal failure have been reported in patients who received micafungin for injection. In fluconazole-controlled trials, the incidence of drug-related renal adverse reactions was 0.4% for micafungin for injection-treated patients and 0.5% for fluconazole-treated patients. Patients who develop abnormal renal function tests during Micafungin for Injection therapy should be monitored for evidence of worsening renal function.

5.5 Infusion and Injection Site Reactions

Possible histamine-mediated symptoms have been reported with micafungin for injection, including rash, pruritus, facial swelling, and vasodilatation. Slow the infusion rate if infusion reaction occurs [see Dosage and Administration (2.4)].

Injection site reactions, including phlebitis and thrombophlebitis have been reported, at micafungin for injection doses of 50 to 150 mg/day. These reactions tended to occur more often in patients receiving micafungin for injection via peripheral intravenous administration [see Dosage and Administration (2.4) and Adverse Reactions (6.1)].

6 ADVERSE REACTIONS

The following clinically significant adverse reactions are described elsewhere in the labeling:

- Hypersensitivity Reactions [see Warnings and Precautions (5.1)]
- Hematological Effects [see Warnings and Precautions (5.2)]
- Hepatic Effects [see Warnings and Precautions (5.3)]
- Renal Effects [see Warnings and Precautions (5.4)]
- Infusion and Injection Site Reactions [see Warnings and Precautions (5.5)]

6.1 Clinical Trials Experience

Because clinical trials are conducted under widely varying conditions, adverse reaction rates observed in clinical trials of micafungin cannot be directly compared to rates in clinical trials of another drug and may not reflect the rates observed in practice.

The overall safety of micafungin for injection was assessed in 520 healthy volunteers and 3227 adult and pediatric patients who received single or multiple doses of micafungin for injection across 46 clinical trials, including the invasive candidiasis, esophageal candidiasis, and prophylaxis trials. The doses of micafungin for injection administered included doses above and below the recommended doses [see Dosage and Administration (2.1, 2.2)] and ranged from 0.75 mg/kg to 10 mg/kg in pediatric patients and 12.5 mg to 150 mg/day or greater in adults.

Clinical Trials Experience in Adults

In clinical trials with micafungin for injection, 2497/2748 (91%) adult patients experienced at least one adverse reaction.

Candidemia and Other Candida Infections

In a randomized, double-blind trial for treatment of candidemia and other Candida infections, adverse reactions occurred in 183/200 (92%) and 171/193 (89%) patients in the micafungin for injection 100 mg/day and caspofungin (70 mg loading dose followed by 50 mg/day dose) treatment groups, respectively. Selected adverse reactions occurring in 5% or more of the patients and more frequently in the micafungin for injection treatment group, are shown in Table 3.

Table 3. Selected* Adverse Reactions in Adult Patients with Candidemia and Other Candida Infections

Adverse Reactions by System Organ Class† | Micafungin for Injection; 100 mg; n (%) | Caspofungin§; n (%)
Number of Patients | 200 | 193
Gastrointestinal Disorders | 81 (41) | 76 (39)
Diarrhea | 15 (8) | 14 (7)
Vomiting | 18 (9) | 16 (8)
Metabolism and Nutrition Disorders | 77 (39) | 73 (38)
Hypoglycemia | 12 (6) | 9 (5)
Hyperkalemia | 10 (5) | 5 (3)
General Disorders/Administration; Site Conditions | 59 (30) | 51 (26)
Investigations | 36 (18) | 37 (19)
Blood Alkaline Phosphatase; Increased | 11 (6) | 8 (4)
Cardiac Disorders | 35 (18) | 36 (19)
Atrial Fibrillation | 5 (3) | 0

Patient base: all randomized patients who received at least 1 dose of trial drug.

* During IV treatment + 3 days

† Within a system organ class, patients may experience more than 1 adverse reaction.

§ 70 mg loading dose on day 1 followed by 50 mg/day thereafter (caspofungin)

In a second, supportive, randomized, double-blind trial for the treatment of candidemia and other Candida infections, adverse reactions occurred in 245/264 (93%) and 250/265 (94%) adult and pediatric patients in the micafungin for injection (100 mg/day) and amphotericin B liposome (3 mg/kg/day) treatment groups, respectively. In this trial, the following adverse reactions were reported in patients at least 16 years of age in the micafungin for injection and amphotericin B liposome treatment groups, respectively: nausea (10% vs. 8%); diarrhea (11% vs. 11%), vomiting (13% vs. 9%), abnormal liver tests (4% vs. 3%); increased aspartate aminotransferase (3% vs. 2%), and increased blood alkaline phosphatase (3% vs. 2%).

Esophageal Candidiasis

In a randomized, double-blind study for treatment of esophageal candidiasis, a total of 202/260 (78%) patients who received micafungin for injection 150 mg/day and 186/258 (72%) patients who received intravenous fluconazole 200 mg/day experienced an adverse reaction. Adverse reactions resulting in discontinuation were reported in 17 (7%) micafungin for injection-treated patients; and in 12 (5%) fluconazole-treated patients. Selected treatment-emergent adverse reactions occurring in 5% or more of the patients and more frequently in the micafungin for injection group, are shown in Table 4.

Table 4. Selected* Adverse Reactions in Adult Patients with Esophageal Candidiasis

Adverse Reactions by System Organ Class† | Micafungin for Injection; 150 mg/day; n (%) | Fluconazole; 200 mg/day n (%)
Number of Patients | 260 | 258
Gastrointestinal Disorders | 84 (32) | 93 (36)
Diarrhea | 27 (10) | 29 (11)
Nausea | 20 (8) | 23 (9)
Vomiting | 17 (7) | 17 (7)
General Disorders/Administration Site Conditions | 52 (20) | 45 (17)
Pyrexia | 34 (13) | 21 (8)
Nervous System Disorders | 42 (16) | 40 (16)
Headache | 22 (9) | 20 (8)
Vascular Disorders | 54 (21) | 21 (8)
Phlebitis | 49 (19) | 13 (5)
Skin and Subcutaneous Tissue Disorders | 36 (14) | 26 (10)
Rash | 14 (5) | 6 (2)

Patient base: all randomized patients who received at least 1 dose of trial drug.

* During treatment + 3 days.

†Within a system organ class, patients may experience more than 1 adverse reaction.

Prophylaxis of Candida Infections in Hematopoietic Stem Cell Transplant Recipients

A double-blind trial was conducted in a total of 882 patients scheduled to undergo an autologous or allogeneic hematopoietic stem cell transplant. The median duration of treatment was 18 days (range 1 to 51 days) in both treatment arms.

All adult patients who received micafungin for injection (382) or fluconazole (409) experienced at least one adverse reaction during the study. Treatment-emergent adverse reactions resulting in micafungin for injection discontinuation were reported in 15 (4%) adult patients; while those resulting in fluconazole discontinuation were reported in 32 (8%). Selected adverse reactions reported in 15% or more of adult patients and more frequently on the micafungin for injection treatment arm, are shown in Table 5.

Table 5. Selected Adverse Reactions in Adult Patients During Prophylaxis of Candida Infection in Hematopoietic Stem Cell Transplant Recipients

System Organ Class | Micafungin for Injection; 50 mg/day; n (%) | Fluconazole; 400 mg/day n (%)
Number of Patients | 382 | 409
Gastrointestinal Disorders | 377 (99) | 404 (99)
Diarrhea | 294 (77) | 327 (80)
Nausea | 270 (71) | 290 (71)
Vomiting | 252 (66) | 274 (67)
Abdominal Pain | 100 (26) | 93 (23)
Blood and Lymphatic System Disorders | 368 (96) | 385 (94)
Neutropenia | 288 (75) | 297 (73)
Thrombocytopenia | 286 (75) | 280 (69)
Skin and Subcutaneous Tissue Disorders | 257 (67) | 275 (67)
Rash | 95 (25) | 91 (22)
Nervous System Disorders | 250 (65) | 254 (62)
Headache | 169 (44) | 154 (38)
Psychiatric Disorders | 233 (61) | 235 (58)
Insomnia | 142 (37) | 140 (34)
Anxiety | 84 (22) | 87 (21)
Cardiac Disorders | 133 (35) | 138 (34)
Tachycardia | 99 (26) | 91 (22)

Patient base: all randomized adult patients who received at least 1 dose of trial drug.

Other selected adverse reactions reported at less than 5% in adult clinical trials are listed below:

- Blood and lymphatic system disorders: coagulopathy, pancytopenia, thrombotic thrombocytopenic purpura
- Cardiac disorders: cardiac arrest, myocardial infarction, pericardial effusion
- General disorders and administration site conditions: infusion reaction, injection site thrombosis
- Hepatobiliary disorders: hepatocellular damage, hepatomegaly, jaundice, hepatic failure
- Immune disorders: hypersensitivity, anaphylactic reaction
- Metabolism and nutrition disorders: hypernatremia, hypokalemia
- Nervous system disorders: convulsions, encephalopathy, intracranial hemorrhage
- Psychiatric disorders: delirium
- Skin and subcutaneous tissue disorders: urticaria

Clinical Trials Experience in Pediatric Patients

The safety of micafungin for injection was assessed in 479 pediatric patients through 16 years of age who received at least one dose of micafungin for injection across 11 clinical trials.

Of the 479 pediatric patients through 16 years of age enrolled in 11 clinical trials, 264 (55%) were male, 319 (67%) were white, with the following age distribution: 116 (24%) <2 years, 108 (23%) 2 to 5 years, 140 (29%) 6 to 11 years, and 115 (24%) 12 to 16 years of age. The mean treatment duration was 24.8 days. A total of 246 patients received at least one dose of micafungin for injection ranging from 2 to 10 mg/kg. Overall, 439/479 (92%) patients experienced at least one adverse reaction. Adverse reactions occurring in ≥15% or more of micafungin-treated pediatric patients were: vomiting (31%), diarrhea (22%), pyrexia (22%), nausea (19%), abdominal pain (16%), and thrombocytopenia (15%).

Two randomized, double-blind active-controlled trials included pediatric patients. In the invasive candidiasis/candidemia trial, the efficacy and safety of micafungin for injection (2 mg/kg/day for patients weighing 40 kg or less and 100 mg/day for patients weighing greater than 40 kg) was compared to amphotericin B liposome (3 mg/kg/day) in 112 pediatric patients. Treatment-emergent adverse reactions occurred in 51/56 (91%) of patients in the micafungin for injection group and 52/56 (93%) of patients in the amphotericin B liposome group. Treatment-emergent adverse reactions resulting in drug discontinuation were reported in 2 (4%) micafungin for injection -treated pediatric patients and in 9 (16%) amphotericin B liposome-treated pediatric patients.

The prophylaxis study in patients undergoing HSCT investigated the efficacy of micafungin for injection (1 mg/kg/day for patients weighing 50 kg or less and 50 mg/day for patients weighing greater than 50 kg) as compared to fluconazole (8 mg/kg/day for patients weighing 50 kg or less and 400 mg/day for patients weighing greater than 50 kg). All 91 pediatric patients experienced at least one treatment-emergent adverse reaction. Three (7%) pediatric patients discontinued micafungin for injection due to adverse reaction; while one (2%) patient discontinued fluconazole.

Selected adverse reactions, occurring in 15% or more of the patients and more frequently in a micafungin for injection group, for the two comparative trials are shown in Table 6.

Table 6. Selected Adverse Reactions in Pediatric Patients with Candidemia and Other Candida Infections (C/IC), and in Hematopoietic Stem-Cell Recipients During Prophylaxis of Candida Infections

Adverse Reactions† | C/IC* |  | Prophylaxis
Adverse Reactions† | Micafungin for Injection; n = 56; n (%) | Amphotericin B; liposome; n = 56; n (%) | Micafungin for Injection; n = 43; n (%) | Fluconazole; n = 48; n (%)
Gastrointestinal disorders | 22 (40) | 18 (32) | 43 (100) | 45 (94)
Vomiting | 10 (18) | 8 (14) | 28 (65) | 32 (67)
Diarrhea | 4 (7) | 5 (9) | 22 (51) | 31 (65)
Nausea | 4 (7) | 4 (7) | 30 (70) | 25 (52)
Abdominal pain | 2 (4) | 2 (4) | 15 (35) | 12 (25)
Abdominal distension | 1 (2) | 1 (2) | 8 (19) | 6 (13)
General disorders and administration site conditions | 14 (25) | 14 (25) | 41 (95) | 46 (96)
Pyrexia | 5 (9) | 9 (16) | 26 (61) | 31 (65)
Infusion-related reaction | 0 | 3 (5) | 7 (16) | 4 (8)
Skin and subcutaneous tissue disorders | 11 (20) | 8 (14) | 33 (77) | 38 (79)
Pruritus | 0 | 1 (2) | 14 (33) | 15 (31)
Rash | 1 (2) | 1 (2) | 13 (30) | 13 (27)
Urticaria | 0 | 1 (2) | 8 (19) | 4 (8)
Respiratory, thoracic and mediastinal disorders | 9 (16) | 13 (23) | 30 (70) | 33 (69)
Epistaxis | 0 | 0 | 4 (9) | 8 (17)
Blood and lymphatic system disorders | 17 (30) | 13 (23) | 40 (93) | 44 (92)
Thrombocytopenia | 5 (9) | 3 (5) | 31 (72) | 37 (77)
Neutropenia | 3 (5) | 4 (7) | 33 (77) | 34 (71)
Anemia | 10 (18) | 6 (11) | 22 (51) | 24 (50)
Febrile neutropenia | 0 | 0 | 7 (16) | 7 (15)
Investigations | 12 (21) | 8 (14) | 24 (56) | 25 (52)
Alanine aminotransferase increased | 0 | 0 | 7 (16) | 1 (2)
Urine output decreased | 0 | 0 | 10 (23) | 8 (17)
Cardiac disorders | 7 (13) | 3 (5) | 10 (23) | 17 (35)
Tachycardia | 2 (4) | 1 (2) | 7 (16) | 12 (25)
Renal and urinary disorders | 4 (7) | 4 (7) | 16 (37) | 15 (31)
Hematuria | 0 | 0 | 10 (23) | 7 (15)
Psychiatric disorders | 3 (5) | 1 (2) | 20 (47) | 9 (19)
Anxiety | 0 | 0 | 10 (23) | 3 (6)

* Study population included 20 pediatric patients younger than 4 months of age (10 in each arm).

† Within a system organ class, patients may experience more than 1 adverse reaction.

Other clinically significant adverse reactions reported at less than 15% in pediatric clinical trials are listed below:

- Hepatobiliary disorders: hyperbilirubinemia
- Investigations: liver tests abnormal
- Renal Disorders: renal failure

Additional pediatric use information is approved for Astellas Pharma US, Inc.’s Mycamine® (micafungin for injection). However, due to Astellas Pharma US, Inc.’s marketing exclusivity rights, this drug product is not labeled with that information.

6.2 Postmarketing Experience

The following adverse reactions have been identified during the post-approval use of micafungin for injection. Because these reactions are reported voluntarily from a population of uncertain size, it is not always possible to reliably estimate their frequency or establish a causal relationship to drug exposure.

- Blood and lymphatic system disorders: disseminated intravascular coagulation
- Hepatobiliary disorders: hepatic disorder
- Renal and urinary disorders: renal impairment
- Skin and subcutaneous tissue disorders: Stevens-Johnson syndrome, toxic epidermal necrolysis
- Vascular disorders: shock

7 DRUG INTERACTIONS

7.1 Effect of Other Drugs on Micafungin for Injection

CYP3A4, CYP2C9 and CYP2C19 Inhibitors

Co-administration of micafungin for injection with cyclosporine, itraconazole, voriconazole and fluconazole did not alter the pharmacokinetics of micafungin.

CYP2C19 and CYP3A4 Inducer

Co-administration of micafungin for injection with rifampin and ritonavir did not alter the pharmacokinetics of micafungin.

Co-administration of Micafungin with Other Drugs

Co-administration of micafungin for injection with mycophenolate mofetil (MMF), amphotericin B, tacrolimus, prednisolone, sirolimus and nifedipine did not alter the pharmacokinetics of micafungin for injection.

7.2 Effect of Micafungin for Injection on Other Drugs

CYP3A4 Substrates

There was no effect of single or multiple doses of micafungin for injection on cyclosporine, tacrolimus, prednisolone, voriconazole and fluconazole pharmacokinetics.

Sirolimus AUC was increased by 21% with no effect on Cmax in the presence of steady-state micafungin for injection compared with sirolimus alone. Nifedipine AUC and Cmax were increased by 18% and 42%, respectively, in the presence of steady-state micafungin compared with nifedipine alone. Itraconazole AUC and Cmax were increased by 22% and 11%, respectively. Patients receiving sirolimus, nifedipine, and itraconazole in combination with Micafungin for Injection should be monitored for sirolimus, nifedipine, and itraconazole toxicity and the sirolimus, nifedipine, and itraconazole dosage should be reduced if necessary.

UDP-Glycosyltransferase Substrate

Co-administration of mycophenolate mofetil (MMF) with micafungin for injection did not alter the pharmacokinetics of MMF.

8 USE IN SPECIFIC POPULATIONS

8.1 Pregnancy

Risk Summary

Based on findings from animal studies, Micafungin for Injection may cause fetal harm when administered to a pregnant woman (see Data). There is insufficient human data on the use of micafungin for injection in pregnant women to inform a drug-associated risk of adverse developmental outcomes. In animal reproduction studies, intravenous administration of micafungin sodium to pregnant rabbits during organogenesis at doses four times the maximum recommended human dose resulted in visceral abnormalities and increased abortion (see Data). Advise pregnant women of the risk to the fetus.

The estimated background risk of major birth defects and miscarriage for the indicated populations is unknown. All pregnancies have a background risk of birth defect, loss, or other adverse outcomes. In the U.S. general population, the estimated background risk of major birth defects and miscarriage in clinically recognized pregnancies is 2 to 4% and 15 to 20%, respectively.

Data

Animal data

In an embryo-fetal toxicity study in pregnant rabbits, intravenous administration of micafungin sodium during organogenesis (days 6 to 18 of gestation) resulted in visceral abnormalities and abortion at 32 mg/kg, a dose equivalent to about four times the recommended dose based on body surface area comparisons. Visceral abnormalities included abnormal lobation of the lung, levocardia, retrocaval ureter, anomalous right subclavian artery, and dilatation of the ureter.

8.2 Lactation

Risk Summary

There are no data on the presence of micafungin in human milk, the effects on the breast-fed infant or the effects on milk production. Micafungin was present in the milk of lactating rats following intravenous administration. When a drug is present in animal milk, it is likely that the drug will be present in human milk. The developmental and health benefits of breastfeeding should be considered along with the mother’s clinical need for Micafungin for Injection, and any potential adverse effects on the breast-fed child from Micafungin for Injection, or from the underlying maternal condition.

8.4 Pediatric Use

Pediatric Patients 4 Months of Age and Older

The safety and effectiveness of micafungin for injection for the treatment of esophageal candidiasis, candidemia, acute disseminated candidiasis, Candida peritonitis and abscesses, esophageal candidiasis, and for prophylaxis of Candida infections in patients undergoing HSCT have been established in pediatric patients 4 months of age and older. Use of micafungin for injection for these indications and in this age group is supported by evidence from adequate and well-controlled studies in adult and pediatric patients with additional pharmacokinetic and safety data in pediatric patients 4 months of age and older [see Indications and Usage (1), Adverse Reactions (6.1), Clinical Pharmacology (12.3), and Clinical Studies (14)].

Pediatric Patients Younger than 4 Months of Age

The safety and effectiveness of micafungin for injection have not been established for the treatment of candidemia with meningoencephalitis and/or ocular dissemination in pediatric patients younger than 4 months of age. In a rabbit model of hematogenous Candida meningoencephalitis (HCME) with Candida albicans (minimum inhibitory concentration of 0.125 mcg/mL), a decrease in mean fungal burden in central nervous system (CNS) compartments assessed as the average of combined fungal burden in the cerebrum, cerebellum, and spinal cord relative to untreated controls, was observed with increasing micafungin dosages administered once daily for 7 days. In this rabbit model, micafungin concentrations could not be reliably detected in cerebrospinal fluid (CSF). Due to limitations of the study design, the clinical significance of a decreased CNS fungal burden in the rabbit HCME model is uncertain.

The safety and effectiveness of micafungin for injection in pediatric patients younger than 4 months of age have not been established for the:

- Treatment of esophageal candidiasis

- Prophylaxis of Candida infections in patients undergoing hematopoietic stem cell transplantation

Additional pediatric use information is approved for Astellas Pharma US, Inc.’s Mycamine® (micafungin for injection). However, due to Astellas Pharma US, Inc.’s marketing exclusivity rights, this drug product is not labeled with that information.

8.5 Geriatric Use

A total of 418 subjects in clinical studies of micafungin for injection were 65 years of age and older, and 124 subjects were 75 years of age and older. No overall differences in safety and effectiveness were observed between these subjects and younger subjects. Other reported clinical experience has not identified differences in responses between the elderly and younger patients, but greater sensitivity of some older individuals cannot be ruled out.

The exposure and disposition of a 50 mg micafungin for injection dose administered as a single 1-hour infusion to 10 healthy subjects aged 66 to 78 years were not significantly different from those in 10 healthy subjects aged 20 to 24 years. No dose adjustment is necessary for the elderly.

8.6 Use in Patients with Renal Impairment

Micafungin for Injection does not require dose adjustment in patients with renal impairment. Supplementary dosing should not be required following hemodialysis [see Clinical Pharmacology (12.3)].

8.7 Use in Patients with Hepatic Impairment

Dose adjustment of Micafungin for Injection is not required in patients with mild, moderate, or severe hepatic impairment [see Clinical Pharmacology (12.3)].

8.8 Race and Gender

No dose adjustment of Micafungin for Injection is required based on gender or race. After 14 daily doses of 150 mg to healthy subjects, micafungin AUC in women was greater by approximately 23% compared with men, due to smaller body weight. No notable differences among white, black, and Hispanic subjects were seen. The micafungin AUC was greater by 19% in Japanese subjects compared to blacks, due to smaller body weight.

9 DRUG ABUSE AND DEPENDENCE

There has been no evidence of either psychological or physical dependence or withdrawal or rebound effects with micafungin for injection.

10 OVERDOSAGE

Micafungin for injection is highly protein bound and, therefore, is not dialyzable. No cases of micafungin for injection overdosage have been reported. Repeated daily doses up to 8 mg/kg (maximum total dose of 896 mg) in adult patients, up to 6 mg/kg in pediatric patients 4 months of age and older, and up to 10 mg/kg in pediatric patients younger than 4 months of age have been administered in clinical trials with no reported dose-limiting toxicity [see Adverse Reactions (6.1)].

Additional pediatric use information is approved for Astellas Pharma US, Inc.’s Mycamine® (micafungin for injection). However, due to Astellas Pharma US, Inc.’s marketing exclusivity rights, this drug product is not labeled with that information.

11 DESCRIPTION

Micafungin for injection is a sterile, lyophilized product for intravenous (IV) infusion that contains micafungin sodium. Micafungin sodium is a semisynthetic lipopeptide (echinocandin) synthesized by a chemical modification of a fermentation product of Coleophoma empetri F-11899. Micafungin inhibits the synthesis of 1, 3-beta-D-glucan, an integral component of the fungal cell wall.

Each single-dose vial contains 50 mg micafungin (equivalent to 50.86 mg micafungin sodium) and 200 mg sucrose or 100 mg micafungin (equivalent to 101.73 mg micafungin sodium) and 400 mg sucrose, with citric acid and/or sodium hydroxide (used for pH adjustment). Micafungin for injection must be diluted with 0.9% Sodium Chloride Injection, USP, or 5% Dextrose Injection, USP [see Dosage and Administration (2.3)]. Following reconstitution with 0.9% Sodium Chloride Injection, USP, the resulting pH of the solution is between 4.5 to 7.0.

Micafungin sodium is chemically designated as:

Pneumocandin A0,1-[(4R,5R)-4,5-dihydroxy-N^2-[4-[5-[4-(pentyloxy)phenyl]-3-isoxazolyl]benzoyl]-L-ornithine]-4-[(4S)-4-hydroxy-4-[4-hydroxy-3-(sulfooxy)phenyl]-L-threonine]-, monosodium salt.

The chemical structure of micafungin sodium is:

The empirical/molecular formula is C56H70N9NaO23S and the formula weight is 1292.26.

Micafungin sodium is a light-sensitive, hygroscopic white powder that is freely soluble in water, isotonic sodium chloride solution, N,N-dimethylformamide and dimethylsulfoxide, slightly soluble in methyl alcohol, and practically insoluble in acetonitrile, ethyl alcohol (95%), acetone, diethyl ether and n-hexane.

12 CLINICAL PHARMACOLOGY

12.1 Mechanism of Action

Micafungin is a member of the echinocandin class of antifungal agents [see Microbiology (12.4)].

12.2 Pharmacodynamics

The pharmacodynamics of micafungin related to hematogenous Candida meningoencephalitis are described in other sections of the prescribing information [see Use in Specific Populations (8.4) and Microbiology (12.4)].

12.3 Pharmacokinetics

Adults

The pharmacokinetics of micafungin were determined in healthy subjects, hematopoietic stem cell transplant recipients, and patients with esophageal candidiasis up to a maximum daily dose of 8 mg/kg body weight.

The relationship of area under the concentration-time curve (AUC) to micafungin dose was linear over the daily dose range of 50 mg to 150 mg and 3 mg/kg to 8 mg/kg body weight. Typically, 85% of the steady-state concentration is achieved after three daily micafungin for injection doses.

Steady-state pharmacokinetic parameters in relevant patient populations after repeated daily administration are presented in Table 7.

Table 7. Pharmacokinetic Parameters of Micafungin in Adult Patients

Population | n | Dose; (mg) | Pharmacokinetic Parameters; (Mean ± Standard Deviation)
Population | n | Dose; (mg) | Cmax; (mcg/mL) | AUC 0-24*; (mcg·h/mL) | t1/2; (h) | Cl; (m L/min/kg)
Patients with IC†; [Day 1]; [Steady State] | 20; 20 | 100; 100 | 5.7±2.2; 10.1±4.4 | 83±51; 97±29 | 14.5±7.0; 13.4±2.0 | 0.359 ±0.179; 0.298 ±0.115
HIV‡- Positive; Patients with EC§; [Day 1]; [Day 14 or 21] | 20; 20; 14; 20; 20; 14 | 50; 100; 150; 50; 100; 150 | 4.1±1.4; 8.0±2.4; 11.6±3.1; 5.1±1.0; 10.1±2.6; 16.4±6.5 | 36±9; 108±31; 151±45; 54±13; 115±25; 167±40 | 14.9±4.3; 13.8±3.0; 14.1±2.6; 15.6±2.8; 16.9±4.4; 15.2±2.2 | 0.321 ±0.098; 0.327 ±0.093; 0.340 ±0.092; 0.300±0.063; 0.301±0.086; 0.297±0.081
HSCT¶ Recipients; [Day 7] | 8; 10; 8; 8 | per kg; 3; 4; 6; 8 | 21.1±2.84; 29.2±6.2; 38.4±6.9; 60.8±26.9 | 234±34; 339±72; 479±157; 663±212 | 14.0±1.4; 14.2±3.2; 14.9±2.6; 17.2±2.3 | 0.214±0.031; 0.204±0.036; 0.224±0.064; 0.223±0.081

* AUC0-infinity is presented for day 1; AUC0-24 is presented for steady state.

† candidemia or other Candida infections.

‡ human immunodeficiency virus.

§ esophageal candidiasis.

¶ hematopoietic stem cell transplant.

Pediatric Patients 4 months of age and older

Micafungin pharmacokinetics in 229 pediatric patients 4 months through 16 years of age were characterized using population pharmacokinetics. Micafungin exposure was dose proportional across the dose and age range studied.

Table 8. Summary (Mean +/- Standard Deviation) of Micafungin Pharmacokinetics in Pediatric Patients 4 Months of Age and Older (Steady-State)

Body weight; group | N | Dose*; mg/kg | Cmax.ss†; (mcg/mL) | AUC.ss†; (mcg·h /mL) | t1/2‡; (h) | CL‡; (m L/min/kg)
30 kg or less | 149 | 1.0 | 7.1 +/- 4.7 | 55 +/- 16 | 12.5 +/- 4.6 | 0.328 +/- 0.091
30 kg or less | 149 | 2.0 | 14.2 +/- 9.3 | 109 +/- 31 | 12.5 +/- 4.6 | 0.328 +/- 0.091
30 kg or less | 149 | 3.0 | 21.3 +/- 14.0 | 164 +/- 47 | 12.5 +/- 4.6 | 0.328 +/- 0.091
Greater than 30 kg | 80 | 1.0 | 8.7 +/- 5.6 | 67 +/- 17 | 13.6 +/- 8.8 | 0.241 +/- 0.061
Greater than 30 kg | 80 | 2.0 | 17.5 +/- 11.2 | 134 +/- 33 | 13.6 +/- 8.8 | 0.241 +/- 0.061
Greater than 30 kg | 80 | 2.5 | 23.0 +/- 14.5 | 176 +/- 42 | 13.6 +/- 8.8 | 0.241 +/- 0.061

* Or the equivalent if receiving the adult dose (50, 100, or 150 mg).

† Derived from simulations from the population PK model.

‡ Derived from the population PK model.

Specific Populations

Adult Patients with Renal Impairment

Micafungin for injection does not require dose adjustment in patients with renal impairment. A single 1-hour infusion of 100 mg micafungin for injection was administered to 9 adult subjects with severe renal impairment (creatinine clearance less than 30 mL/min) and to 9 age-, gender-, and weight-matched subjects with normal renal function (creatinine clearance greater than 80 mL/min). The maximum concentration (Cmax) and AUC were not significantly altered by severe renal impairment.

Since micafungin is highly protein bound, it is not dialyzable. Supplementary dosing should not be required following hemodialysis.

Adult Patients with Hepatic Impairment

- A single 1-hour infusion of 100 mg micafungin for injection was administered to 8 adult subjects with moderate hepatic impairment (Child-Pugh score 7 to 9) and 8 age-, gender-, and weight-matched subjects with normal hepatic function. The Cmax and AUC values of micafungin were lower by approximately 22% in subjects with moderate hepatic impairment compared to normal subjects. This difference in micafungin exposure does not require dose adjustment of micafungin for injection in patients with moderate hepatic impairment.
- A single 1-hour infusion of 100 mg micafungin for injection was administered to 8 adult subjects with severe hepatic impairment (Child-Pugh score 10 to 12) and 8 age-, gender-, ethnic- and weight-matched subjects with normal hepatic function. The mean Cmax and AUC values of micafungin were lower by approximately 30% in subjects with severe hepatic impairment compared to normal subjects. The mean Cmax and AUC values of M-5 metabolite were approximately 2.3-fold higher in subjects with severe hepatic impairment compared to normal subjects; however, this exposure (parent and metabolite) was comparable to that in patients with systemic Candida infection. Therefore, no micafungin for injection dose adjustment is necessary in patients with severe hepatic impairment.

Distribution

The mean ± standard deviation volume of distribution of micafungin at terminal phase was 0.39 ± 0.11 L/kg body weight when determined in adult patients with esophageal candidiasis at the dose range of 50 mg to 150 mg.

Micafungin is highly (greater than 99%) protein bound in vitro, independent of plasma concentrations over the range of 10 to 100 mcg/mL. The primary binding protein is albumin; however, micafungin, at therapeutically relevant concentrations, does not competitively displace bilirubin binding to albumin. Micafungin also binds to a lesser extent to α1-acid-glycoprotein.

Micafungin is neither a substrate nor an inhibitor of P-glycoprotein.

Metabolism

Micafungin is metabolized to M-1 (catechol form) by arylsulfatase, with further metabolism to M-2 (methoxy form) by catechol-O-methyltransferase. M-5 is formed by hydroxylation at the side chain (ω-1 position) of micafungin catalyzed by cytochrome P450 (CYP) isozymes. Even though micafungin is a substrate for and a weak inhibitor of CYP3A in vitro, hydroxylation by CYP3A is not a major pathway for micafungin metabolism in vivo. Micafungin is neither a P- glycoprotein substrate nor inhibitor in vitro.

In four healthy volunteer studies, the ratio of metabolite to parent exposure (AUC) at a dose of 150 mg/day was 6% for M-1, 1% for M-2, and 6% for M-5. In patients with esophageal candidiasis, the ratio of metabolite to parent exposure (AUC) at a dose of 150 mg/day was 11% for M-1, 2% for M-2, and 12% for M-5.

Excretion

The excretion of radioactivity following a single intravenous dose of ^14C-micafungin sodium for injection (25 mg) was evaluated in healthy volunteers. At 28 days after administration, mean urinary and fecal recovery of total radioactivity accounted for 82.5% (76.4% to 87.9%) of the administered dose. Fecal excretion is the major route of elimination (total radioactivity at 28 days was 71% of the administered dose).

Additional pediatric use information is approved for Astellas Pharma US, Inc.’s Mycamine® (micafungin for injection). However, due to Astellas Pharma US, Inc.’s marketing exclusivity rights, this drug product is not labeled with that information.

12.4 Microbiology

Mechanism of Action

Micafungin inhibits the synthesis of 1, 3-beta-D-glucan, an essential component of fungal cell walls, which is not present in mammalian cells.

Activity in Animal Models of Candidiasis

Activity of micafungin has been demonstrated in both mucosal and disseminated murine and rabbit models of candidiasis. Micafungin administered to immunocompetent or immunosuppressed mice or rabbits with disseminated candidiasis prolonged survival (mice) and/or decreased the fungal burden in different organs including brain in a dose-dependent manner (mice and rabbits). Overall, antifungal activity of micafungin was demonstrated in the brain and eye tissues of nonneutropenic rabbits with HCME infected with a micafungin-sensitive strain of C. albicans; however, the activity varied in different central nervous system and ocular compartments. In the cerebrum, culture negativity was achieved at a micafungin dose regimen of 32 mg/kg once daily for 7 days; whereas, in spinal cord, vitreous humor, and choroid, culture negativity was achieved at micafungin dose regimens of 24 to 32 mg/kg once daily. Compared to untreated animals, micafungin dose regimens between 8 and 24 mg/kg once daily reduced fungal burden in the cerebrum and cerebellum. When cerebrum, cerebellum and spinal cord data were combined, a decrease in fungal burden relative to untreated controls was evident at micafungin dose regimens between 16 and 32 mg/kg once daily.

Resistance

There have been reports of clinical failures in patients receiving micafungin for injection therapy due to the development of drug resistance. Some of these reports have identified specific mutations in the FKS protein component of the glucan synthase enzyme that are associated with higher MICs and breakthrough infection.

Antimicrobial Activity

Micafungin has been shown to be active against most isolates of the following Candida species, both in vitro and in clinical infections [see Indications and Usage (1)]:

Candida albicans
Candida glabrata
Candida guilliermondii
Candida krusei
Candida parapsilosis
Candida tropicalis

Susceptibility Testing

For specific information regarding susceptibility test interpretive criteria and associated test methods and quality control standards recognized by FDA for this drug, please see: https://www.fda.gov/STIC.

13 NONCLINICAL TOXICOLOGY

13.1 Carcinogenesis, Mutagenesis, Impairment of Fertility

Hepatic carcinomas and adenomas were observed in a 6-month intravenous toxicology study with an 18-month recovery period of micafungin sodium in rats designed to assess the reversibility of hepatocellular lesions.

Rats administered micafungin sodium for 3 months at 32 mg/kg/day (corresponding to 8 times the highest recommended human dose [150 mg/day], based on AUC comparisons), exhibited colored patches/zones, multinucleated hepatocytes and altered hepatocellular foci after 1 or 3-month recovery periods, and adenomas were observed after a 21-month recovery period. Rats administered micafungin sodium at the same dose for 6 months exhibited adenomas after a 12-month recovery period; after an 18-month recovery period, an increased incidence of adenomas was observed, and additionally, carcinomas were detected. A lower dose of micafungin sodium (equivalent to 5 times the human AUC) in the 6-month rat study resulted in a lower incidence of adenomas and carcinomas following 18 months recovery. The duration of micafungin for injection dosing in these rat studies (3 or 6 months) exceeds the usual duration of micafungin dosing in patients, which is typically less than 1 month for treatment of esophageal candidiasis, but dosing may exceed 1 month for Candida prophylaxis.

Although the increase in carcinomas in the 6-month rat study did not reach statistical significance, the persistence of altered hepatocellular foci subsequent to micafungin for injection dosing, and the presence of adenomas and carcinomas in the recovery periods suggest a causal relationship between micafungin sodium, altered hepatocellular foci, and hepatic neoplasms. Whole-life carcinogenicity studies of micafungin for injection in animals have not been conducted, and it is not known whether the hepatic neoplasms observed in treated rats also occur in other species, or if there is a dose threshold for this effect.

Micafungin sodium was not mutagenic or clastogenic when evaluated in a standard battery of in vitro and in vivo tests (i.e., bacterial reversion - S. typhimurium, E. coli; chromosomal aberration; intravenous mouse micronucleus).

Male rats treated intravenously with micafungin sodium for 9 weeks showed vacuolation of the epididymal ductal epithelial cells at or above 10 mg/kg (about 0.6 times the recommended clinical dose for esophageal candidiasis, based on body surface area comparisons). Higher doses (about twice the recommended clinical dose, based on body surface area comparisons) resulted in higher epididymis weights and reduced numbers of sperm cells. In a 39-week intravenous study in dogs, seminiferous tubular atrophy and decreased sperm in the epididymis were observed at 10 and 32 mg/kg, doses equal to about 2 and 7 times the recommended clinical dose, based on body surface area comparisons. There was no impairment of fertility in animal studies with micafungin sodium.

13.2 Animal Toxicology and/or Pharmacology

High doses of micafungin sodium (5 to 8 times the highest recommended human dose, based on AUC comparisons) have been associated with irreversible changes to the liver when administered for 3 or 6 months, and these changes may be indicative of pre-malignant processes [see Nonclinical Toxicology (13.1)].

14 CLINICAL STUDIES

14.1 Treatment of Candidemia and Other Candida Infections in Adult and Pediatric Patients 4 Months of Age and Older

Two dose levels of micafungin for injection were evaluated in a randomized, double-blind study to determine the efficacy and safety versus caspofungin in patients with invasive candidiasis and candidemia. Patients were randomized to receive once daily intravenous infusions (IV) of micafungin for injection, either 100 mg/day or 150 mg/day or caspofungin (70 mg loading dose followed by 50 mg maintenance dose). Patients in both study arms were permitted to switch to oral fluconazole after at least 10 days of intravenous therapy, provided they were non-neutropenic, had improvement or resolution of clinical signs and symptoms, had a Candida isolate which was susceptible to fluconazole, and had documentation of 2 negative cultures drawn at least 24 hours apart. Patients were stratified by APACHE II score (20 or less or greater than 20) and by geographic region. Patients with Candida endocarditis were excluded from this analysis. Outcome was assessed by overall treatment success based on clinical (complete resolution or improvement in attributable signs and symptoms and radiographic abnormalities of the Candida infection and no additional antifungal therapy) and mycological (eradication or presumed eradication) response at the end of IV therapy. Deaths that occurred during IV study drug therapy were treated as failures.

In this study, 111/578 (19.2%) of the patients had baseline APACHE II scores of greater than 20, and 50/578 (8.7%) were neutropenic at baseline (absolute neutrophil count less than 500 cells/mm^3). Outcome, relapse and mortality data are shown for the recommended dose of micafungin for injection (100 mg/day) and caspofungin in Table 9.

Table 9. Efficacy Analysis: Treatment Success in Patients in Study 03-0-192 with Candidemia and Other Candida Infections

 | Micafungin for Injection 100 mg/day; n (%); % treatment difference; (95% CI) | Caspofungin 70/50 mg/day*; n (%)
Treatment Success at End of IV Therapy† | 135/191 (70.7); 7.4; (-2.0, 16.3) | 119/188 (63.3)
Success in Patients with Neutropenia at Baseline | 14/22 (63.6) | 5/11 (45.5)
Success by Site of Infection; Candidemia; Abscess; Acute Disseminated‡; Endophthalmitis; Chorioretinitis; Skin; Kidney; Pancreas; Peritoneum; Lung/Skin; Lung/Spleen; Liver; Intraabdominal abscess; Chronic Disseminated; Peritonitis | 116/163 (71.2); 4/5 (80); 6/13 (46.2); 1/3; 0/3; 1/1; 2/2; 1/1; 1/1; 0/1; 0/1; 0; 0 | 103/161 (64); 5/9 (55.6); 5/9 (55.6); 1/1; 0; 0; 1/1; 0; 0; 0; 0; 0/2; 3/5
Success by Site of Infection; Candidemia; Abscess; Acute Disseminated‡; Endophthalmitis; Chorioretinitis; Skin; Kidney; Pancreas; Peritoneum; Lung/Skin; Lung/Spleen; Liver; Intraabdominal abscess; Chronic Disseminated; Peritonitis | 0/1; 4/6 (66.7) | 0; 2/5 (40)
Success by Organism§; C. albicans; C. glabrata; C. tropicalis; C. parapsilosis; C. krusei; C. guilliermondii; C. lusitaniae | 57/81 (70.4); 16/23 (69.6); 17/27 (63); 21/28 (75); 5/8 (62.5); 1/2; 2/3 (66.7) | 45/73 (61.6); 19/31 (61.3); 22/29 (75.9); 22/39 (56.4); 2/3 (66.7); 0/1; 2/2
Relapse through 6 Weeks¶; Overall; Culture-confirmed relapse; Required systemic antifungal therapy; Died during follow-up; Not assessed | 49/135 (36.3); 5; 11; 17; 16 | 44/119 (37); 4; 5; 16; 19
Overall study mortality; Mortality during IV therapy | 58/200 (29); 28/200 (14) | 51/193 (26.4); 27/193 (14)

* 70 mg loading dose on day 1 followed by 50 mg/day thereafter (caspofungin).

† All patients who received at least one dose of study medication and had documented invasive candidiasis or candidemia. Patients with Candida endocarditis were excluded from the analyses.

‡ A patient may have had greater than 1 organ of dissemination.

§ A patient may have had greater than 1 baseline infection species.

¶ All patients who had a culture-confirmed relapse or required systemic antifungal therapy in the post treatment period for a suspected or proven Candida infection. Also includes patients who died or were not assessed in follow-up.

In two cases of ophthalmic involvement assessed as failures in the above table due to missing evaluation at the end of IV treatment with micafungin for injection, therapeutic success was documented during protocol-defined oral fluconazole therapy.

14.2 Treatment of Esophageal Candidiasis in Adult and Pediatric Patients 4 Months of Age and Older

In two controlled trials involving 763 patients with esophageal candidiasis, 445 adults with endoscopically-proven candidiasis received micafungin for injection, and 318 received fluconazole for a median duration of 14 days (range 1 to 33 days).

Micafungin for injection was evaluated in a randomized, double blind study which compared micafungin for injection 150 mg/day (n = 260) to intravenous fluconazole 200 mg/day (n = 258) in adults with endoscopically-proven esophageal candidiasis. Most patients in this study had HIV infection, with CD4 cell counts less than 100 cells/mm^3. Outcome was assessed by endoscopy and by clinical response at the end of treatment. Endoscopic cure was defined as endoscopic grade 0, based on a scale of 0 to 3. Clinical cure was defined as complete resolution in clinical symptoms of esophageal candidiasis (dysphagia, odynophagia, and retrosternal pain). Overall therapeutic cure was defined as both clinical and endoscopic cure. Mycological eradication was determined by culture, and by histological or cytological evaluation of esophageal biopsy or brushings obtained endoscopically at the end of treatment. As shown in Table 10, endoscopic cure, clinical cure, overall therapeutic cure, and mycological eradication were comparable for patients in the micafungin for injection and fluconazole treatment groups.

Table 10. Endoscopic, Clinical, and Mycological Outcomes for Esophageal Candidiasis at End-of- Treatment

Treatment Outcome* | Micafungin for Injection; 150 mg/day; n = 260 | Fluconazole; 200 mg/day; n = 258 | % Difference†; (95% CI)
Endoscopic Cure | 228 (87.7%) | 227 (88.0%) | -0.3% (-5.9, +5.3)
Clinical Cure | 239 (91.9%) | 237 (91.9%) | 0.06% (-4.6, +4.8)
Overall Therapeutic Cure | 223 (85.8%) | 220 (85.3%) | 0.5% (-5.6, +6.6)
Mycological Eradication | 141/189 (74.6%) | 149/192 (77.6%) | -3.0% (-11.6, +5.6)

* Endoscopic and clinical outcome were measured in modified intent-to-treat population, including all randomized patients who received 1 or more doses of study treatment. Mycological outcome was determined in the per protocol (evaluable) population, including patients with confirmed esophageal candidiasis who received at least 10 doses of study drug, and had no major protocol violations.

† Calculated as micafungin for injection – fluconazole.

Most patients (96%) in this study had C. albicans isolated at baseline. The efficacy of micafungin for injection was evaluated in less than 10 patients with Candida species other than C. albicans, most of which were isolated concurrently with C. albicans.

Relapse was assessed at 2 and 4 weeks post-treatment in patients with overall therapeutic cure at end of treatment. Relapse was defined as a recurrence of clinical symptoms or endoscopic lesions (endoscopic grade greater than 0). There was no statistically significant difference in relapse rates at either 2 weeks or through 4 weeks post-treatment for patients in the micafungin for injection and fluconazole treatment groups, as shown in Table 11.

Table 11. Relapse of Esophageal Candidiasis at Week 2 and through Week 4 Post-Treatment in Patients with Overall Therapeutic Cure at the End of Treatment

Relapse | Micafungin for Injection; 150 mg/day; n = 223 | Fluconazole; 200 mg/day; n = 220 | % Difference*; (95% CI)
Relapse† at Week 2 | 40 (17.9%) | 30 (13.6%) | 4.3% (-2.5, 11.1)
Relapse† through Week 4(cumulative) | 73 (32.7%) | 62 (28.2%) | 4.6% (-4.0, 13.1)

* Calculated as micafungin for injection – fluconazole; N = number of patients with overall therapeutic cure (both clinical and endoscopic cure at end-of-treatment);

† Relapse included patients who died or were lost to follow-up, and those who received systemic anti-fungal therapy in the post-treatment period.

In this study, 459 of 518 (88.6%) patients had oropharyngeal candidiasis in addition to esophageal candidiasis at baseline. At the end of treatment 192/230 (83.5%) micafungin for injection -treated patients and 188/229 (82.1%) of fluconazole treated patients experienced resolution of signs and symptoms of oropharyngeal candidiasis. Of these, 32.3% in the micafungin for injection group, and 18.1% in the fluconazole group (treatment difference = 14.2%; 95% confidence interval [5.6, 22.8]) had symptomatic relapse at 2 weeks post-treatment. Relapse included patients who died or were lost to follow-up, and those who received systemic antifungal therapy during the post-treatment period. Cumulative relapse at 4 weeks post-treatment was 52.1% in the micafungin for injection group and 39.4% in the fluconazole group (treatment difference 12.7%, 95% confidence interval [2.8, 22.7]).

14.3 Prophylaxis of Candida Infections in Hematopoietic Stem Cell Transplant Recipients

In a randomized, double-blind study, micafungin for injection (50 mg IV once daily) was compared to fluconazole (400 mg IV once daily) in 882 [adult (791) and pediatric (91)] patients undergoing an autologous or syngeneic (46%) or allogeneic (54%) stem cell transplant. All pediatric patients, except 2 per group, received allogeneic transplants. The status of the patients’ underlying malignancy at the time of randomization was: 365 (41%) patients with active disease, 326 (37%) patients in remission, and 195 (22%) patients in relapse. The more common baseline underlying diseases in the 476 allogeneic transplant recipients were: chronic myelogenous leukemia (22%), acute myelogenous leukemia (21%), acute lymphocytic leukemia (13%), and non-Hodgkin’s lymphoma (13%). In the 404 autologous and syngeneic transplant recipients the more common baseline underlying diseases were: multiple myeloma (37.1%), non-Hodgkin’s lymphoma (36.4%), and Hodgkin's disease (15.6%). During the study, 198 of 882 (22.4%) transplant recipients had proven graft-versus-host disease; and 475 of 882 (53.9%) recipients received immunosuppressive medications for treatment or prophylaxis of graft-versus-host disease.

Study drug was continued until the patient had neutrophil recovery to an absolute neutrophil count (ANC) of 500 cells/mm^3 or greater or up to a maximum of 42 days after transplant. The average duration of drug administration was 18 days (range 1 to 51 days). Duration of therapy was slightly longer in the pediatric patients who received micafungin for injection (median duration 22 days) compared to the adult patients who received micafungin for injection (median duration 18 days).

Successful prophylaxis was defined as the absence of a proven, probable, or suspected systemic fungal infection through the end of therapy (usually 18 days), and the absence of a proven or probable systemic fungal infection through the end of the 4-week post-therapy period. A suspected systemic fungal infection was diagnosed in patients with neutropenia (ANC less than 500 cells/mm^3); persistent or recurrent fever (while ANC less than 500 cells/mm^3) of no known etiology; and failure to respond to at least 96 hours of broad spectrum antibacterial therapy. A persistent fever was defined as four consecutive days of fever greater than 38ºC. A recurrent fever was defined as having at least one day with temperatures 38.5ºC or higher after having at least one prior temperature higher than 38ºC; or having two days of temperatures higher than 38ºC after having at least one prior temperature higher than 38ºC. Transplant recipients who died or were lost to follow-up during the study were considered failures of prophylactic therapy.

Successful prophylaxis was documented in 80.7% of adult and pediatric micafungin for injection recipients, and in 73.7% of adult and pediatric patients who received fluconazole (7.0% difference [95% CI = 1.5, 12.5]), as shown in Table 12, along with other study endpoints. The use of systemic antifungal therapy post-treatment was 42% in both groups.

The number of proven breakthrough Candida infections was 4 in the micafungin for injection and 2 in the fluconazole group.

The efficacy of micafungin for injection against infections caused by fungi other than Candida has not been established.

Table 12. Results from Clinical Study of Prophylaxis of Candida Infections in Hematopoietic Stem Cell Transplant Recipients

Outcome of Prophylaxis | Micafungin for Injection; 50 mg/day; (n = 425) | Fluconazole; 400 mg/day; (n = 457)
Success* | 343 (80.7%) | 337 (73.7%)
Failure: | 82 (19.3%) | 120 (26.3%)
All Deaths†; Proven/probable fungal infection prior to death | 18 (4.2%); 1 (0.2%) | 26 (5.7%); 3 (0.7%)
Proven/probable fungal infection (not resulting in death)† | 6 (1.4%) | 8 (1.8%)
Suspected fungal infection‡ | 53 (12.5%) | 83 (18.2%)
Lost to follow-up | 5 (1.2%) | 3 (0.7%)

* Difference (micafungin for injection– fluconazole): +7.0% [95% CI=1.5, 12.5].

† Through end-of-study (4 weeks post-therapy).

‡ Through end-of-therapy.

16 HOW SUPPLIED/STORAGE AND HANDLING

Micafungin for Injection is supplied as a sterile, white lyophilized powder for reconstitution for intravenous infusion, and is available in the following packaging configurations:

NDC 42023-229-10: 50 mg single-dose vials supplied in packages of 10

NDC 42023-230-10: 100 mg single-dose vials supplied in packages of 10

The vial stopper is not manufactured with natural rubber latex.

Storage

Store Micafungin for Injection, for intravenous use at room temperature, 20°C to 25°C (68°F to 77°F). [See USP Controlled Room Temperature].

Store the reconstituted product at 25°C (77°F) [see Dosage and Administration (2.3)].

Store the diluted solution at 25°C (77°F) [see Dosage and Administration (2.3)].

Protect from light.

17 PATIENT COUNSELING INFORMATION

Hypersensitivity

Inform patients about the serious adverse effects of Micafungin for Injection including hypersensitivity reactions e.g., anaphylaxis and anaphylactoid reactions including shock.

Hepatic

Inform patients about the serious adverse effects of Micafungin for Injection including hepatic effects e.g., abnormal liver tests, hepatic impairment, hepatitis or worsening hepatic failure.

Hematologic

Inform patients about the serious adverse effects of Micafungin for Injection including hematological effects e.g., acute intravascular hemolysis, hemolytic anemia and hemoglobinuria.

Renal

Inform patients about the serious adverse effects of Micafungin for Injection including renal effects e.g., elevations in BUN and creatinine, renal impairment or acute renal failure.

Embryo-Fetal Toxicity

Advise pregnant women and females of reproductive potential of the potential risk of Micafungin for Injection to a fetus. Advise females to inform their healthcare provider of a known or suspected pregnancy.

Concomitant Medications

Instruct patients to inform their healthcare provider of any other medications they are currently taking with Micafungin for Injection, including over-the-counter medications.

Manufactured for:

Endo USA

Malvern, PA 19355

© 2024 Endo, Inc. or one of its affiliates.

R07/2024